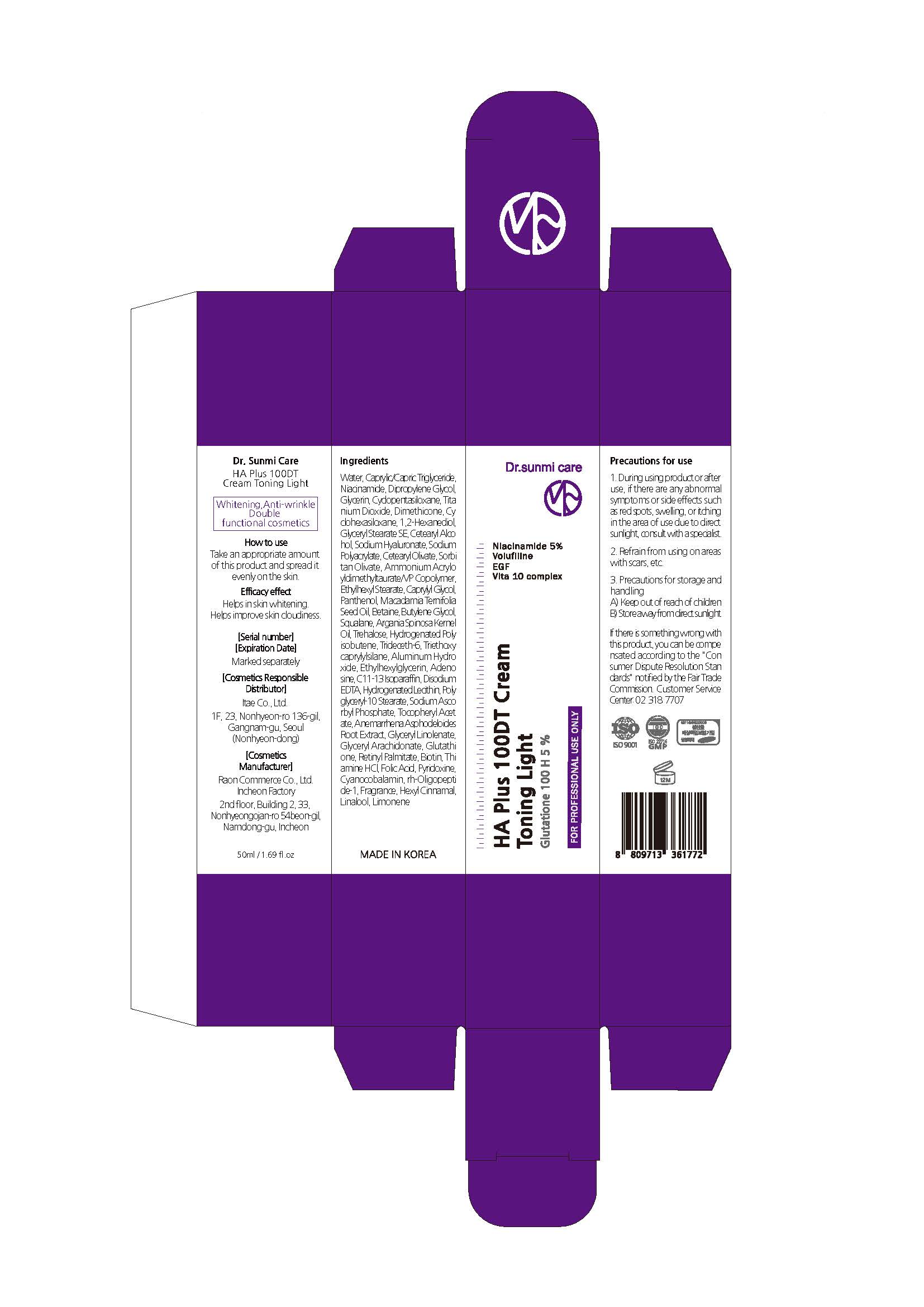 DRUG LABEL: HA Plus 100DT Cream Toning Light
NDC: 82083-0019 | Form: CREAM
Manufacturer: LAON COMMERCE co ltd
Category: otc | Type: HUMAN OTC DRUG LABEL
Date: 20230608

ACTIVE INGREDIENTS: ADENOSINE 0.04 g/100 mL; NIACINAMIDE 5 g/100 mL
INACTIVE INGREDIENTS: WATER

ACTIVE INGREDIENT

Niacinamide, Adenosine

INACTIVE INGREDIENT

Water
Glycerin
PEG-60 Hydrogenated Castor Oil
Disodium Cocoamphodiacetate
1,2-Hexanediol
Cocamidopropyl Betaine
Sodium Laureth Sulfate
Sodium Chloride

Water
Caprylic/Capric Triglyceride
Dipropylene Glycol
Glycerin
Cyclopentasiloxane
Titanium Dioxide
Dimethicone
Cyclohexasiloxane
1,2-Hexanediol
Glyceryl Stearate SE
Cetearyl Alcohol
Sodium Hyaluronate
Sodium Polyacrylate
Cetearyl Olivate
Sorbitan Olivate
Ammonium Acryloyldimethyltaurate/VP Copolymer
Ethylhexyl Stearate
Caprylyl Glycol
Panthenol
Macadamia Ternifolia Seed Oil
Betaine
Butylene Glycol
Squalane
Argania Spinosa Kernel Oil
Trehalose
Hydrogenated Polyisobutene
Trideceth-6
Triethoxycaprylylsilane
Aluminum Hydroxide
Ethylhexylglycerin
C11-13 Isoparaffin
Disodium EDTA
Hydrogenated Lecithin
Polyglyceryl-10 Stearate
Sodium Ascorbyl Phosphate
Tocopheryl Acetate
Anemarrhena Asphodeloides Root Extract
Glyceryl Linolenate
Glyceryl Arachidonate
Glutathione
Retinyl Palmitate
Biotin
Thiamine HCl
Folic Acid
Pyridoxine
Cyanocobalamin
rh-Oligopeptide-1
Fragrance
Hexyl Cinnamal
Linalool
Limonene

Camellia Sinensis Leaf Extract
Bambusa Vulgaris Extract
Rosmarinus Officinalis (Rosemary) Leaf Extract
Chamomilla Recutita (Matricaria) Flower Extract
Centella Asiatica Extract
Salvia Officinalis (Sage) Leaf Extract
Portulaca Oleracea Extract
Nelumbo Nucifera Flower Extract
Olea Europaea (Olive) Fruit Extract
Melaleuca Alternifolia (Tea Tree) Extract
Tremella Fuciformis (Mushroom) Extract
Salix Alba (Willow) Bark Extract
Trehalose
Coco-Betaine
Citric Acid
Sodium Citrate
Ethylhexylglycerin
Disodium EDTA
Fragrance
Hexylene Glycol
Caprylyl Glycol
Butylene Glycol

PURPOSE

skin protect

KEEP OUT OF REACH OF THE CHILDREN

INDICATIONS AND USAGE

Take an appropriate amount of this product and spread it evenly on the skin.

WARNINGS

1. During using product or after use, if there are any abnormal symptoms or side effects such as red spots, swelling or itching in the area of use due to direct sunlight, consult with a specialist.

2. Refrain from using on areas with scars, etc.

3. Precautions for storage and handling

A) Keep out of reach of children

B) Store away from direct sunlight

DOSAGE AND ADMINISTRATION

topical use only